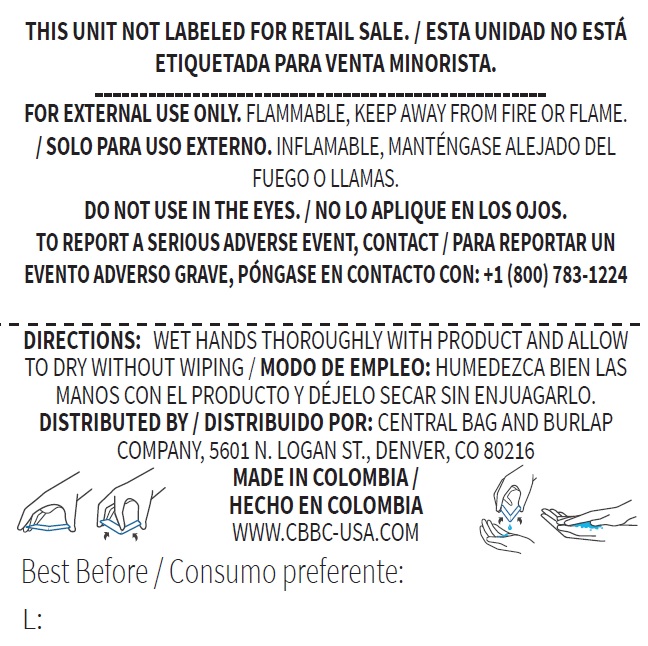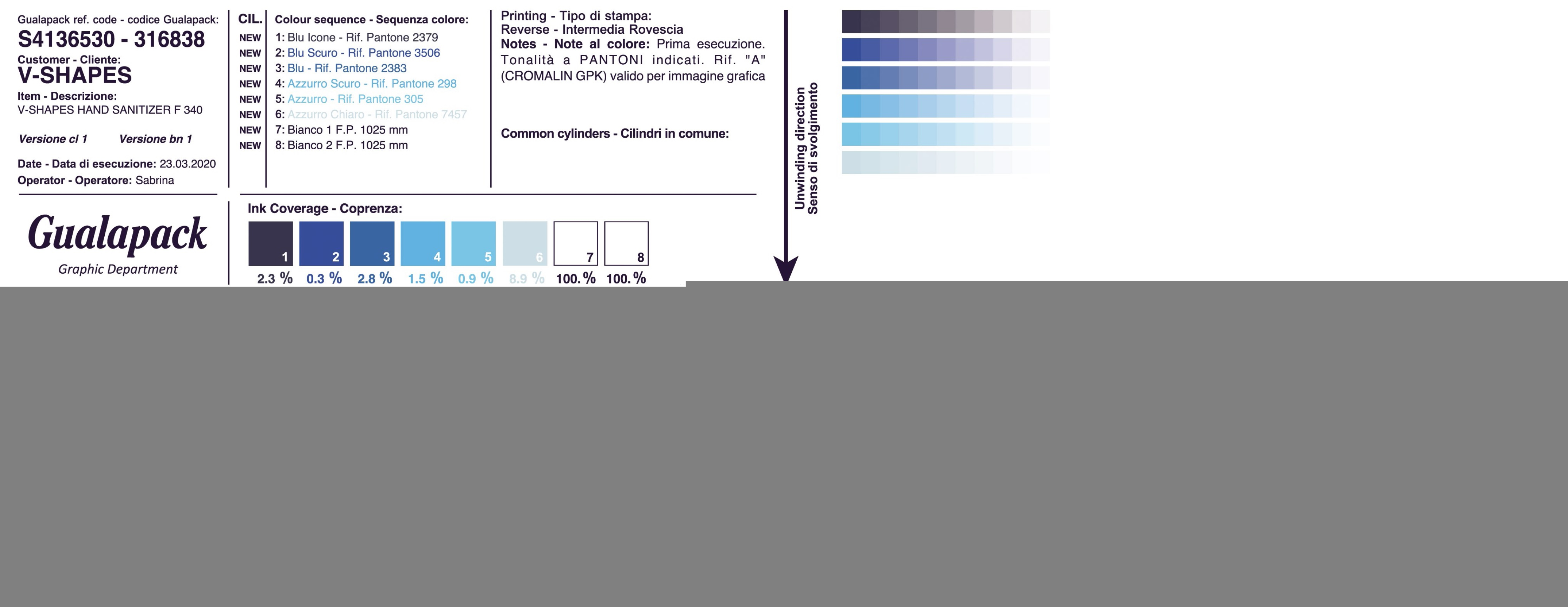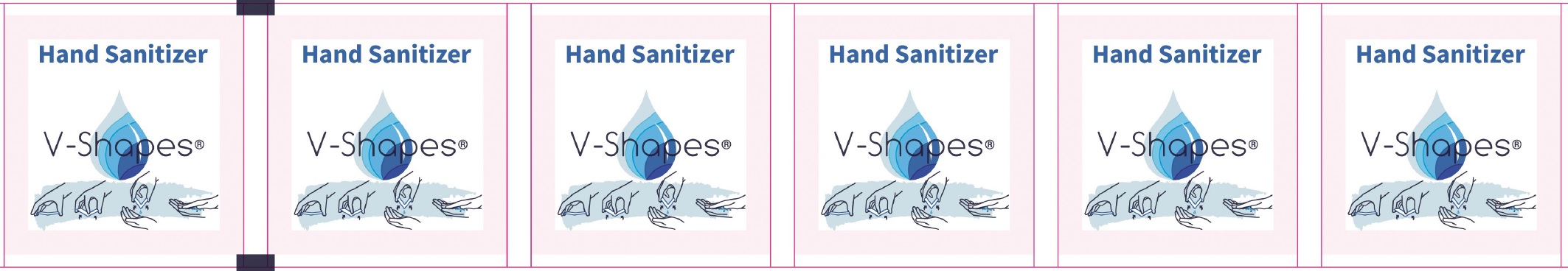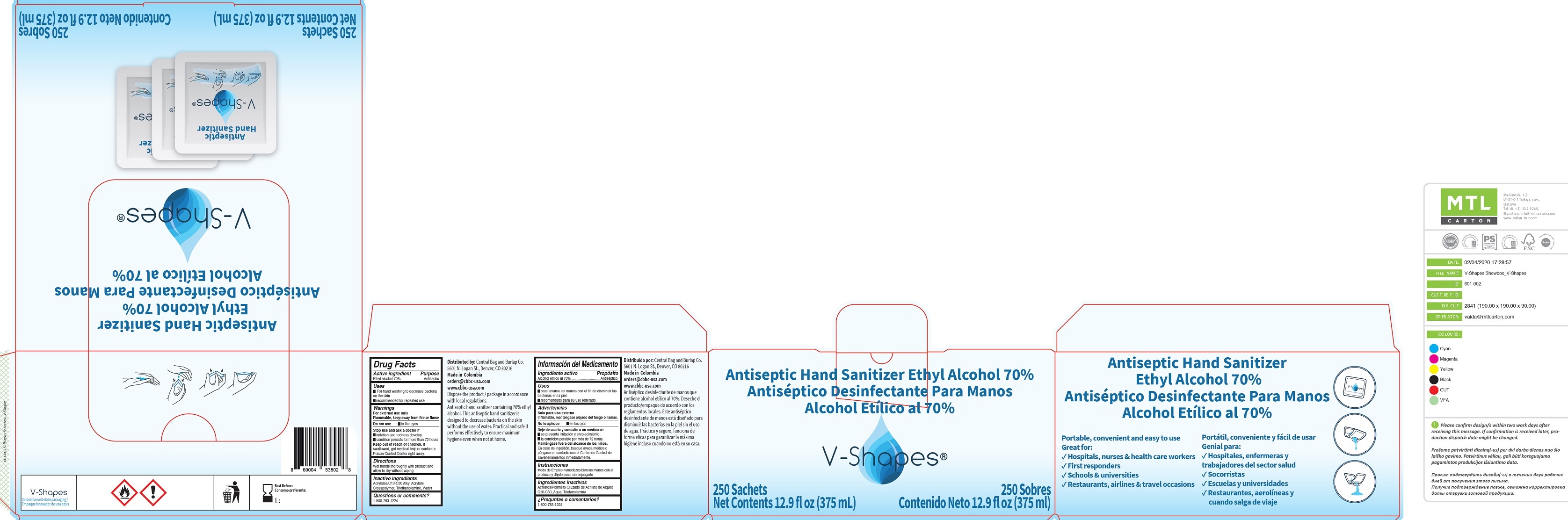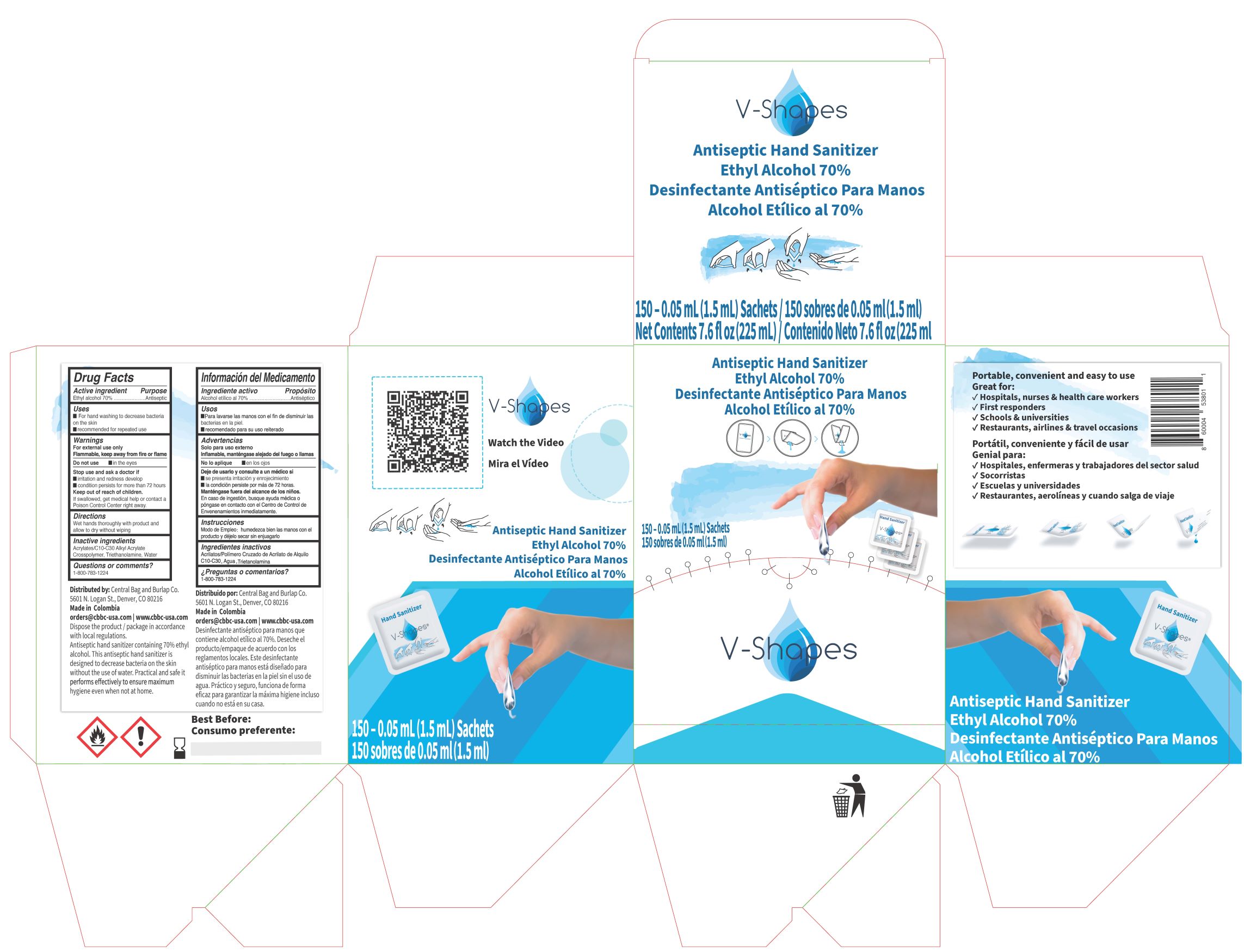 DRUG LABEL: V-Shapes Antiseptic Hand Sanitizer Ethyl Alcohol
NDC: 74785-005 | Form: GEL
Manufacturer: V-SHAPES SRL
Category: otc | Type: HUMAN OTC DRUG LABEL
Date: 20200915

ACTIVE INGREDIENTS: ALCOHOL 0.7 mL/1 mL
INACTIVE INGREDIENTS: CARBOMER INTERPOLYMER TYPE A (ALLYL SUCROSE CROSSLINKED); TROLAMINE; WATER

V-Shapes Antiseptic Hand Sanitizer Ethyl Alcohol

Active ingredient

Ethyl alcohol 70%

Purpose

Antiseptic

Uses

- For hand washing to decrease bacteria on the skin
- recommended for repeated use

Warnings

For external use only

Flammable, keep away from fire or flame.

Do not use

in the eyes

Stop use and ask a doctor if

- irritation and redness develop
- condition persists for more than 72 hours

Keep out of reach of children.

If swallowed, get medical help or contact a Poison Control Center right away.

Directions

Wet hands thoroughly with product and allow to dry without wiping

Inactive ingredients

Acrylates/C10-C30 Alkyl Acrylate Crosspolymer, Triethanolamine, Water

Questions or comments?

1-800-783-1224